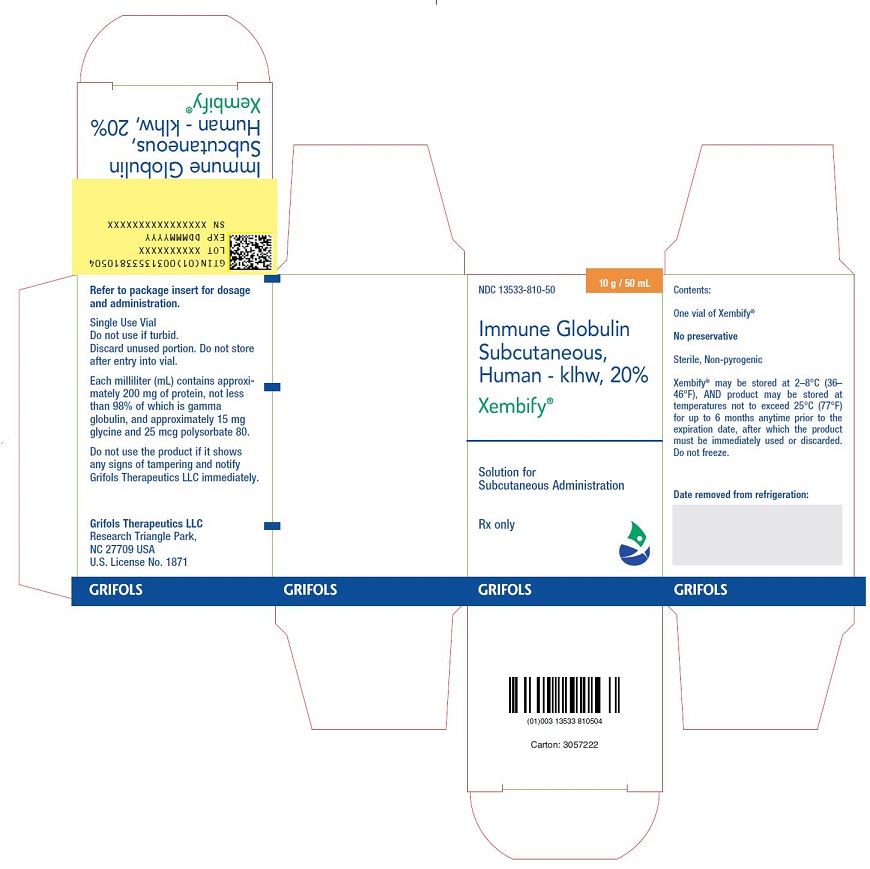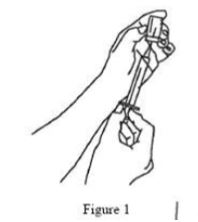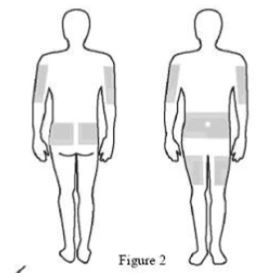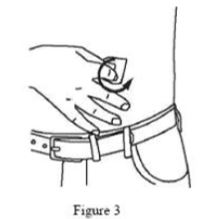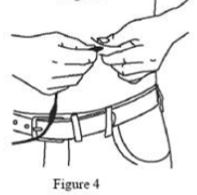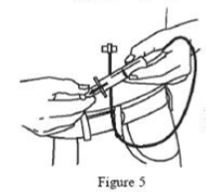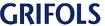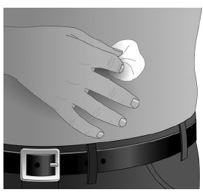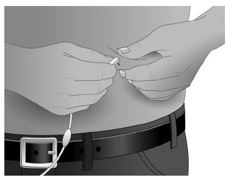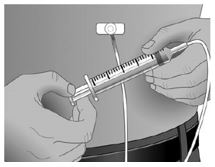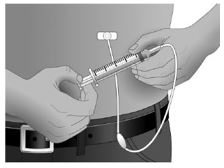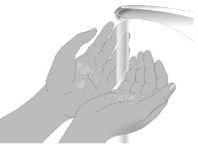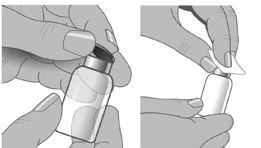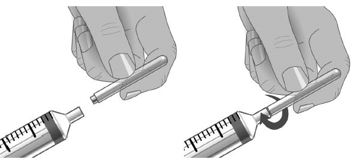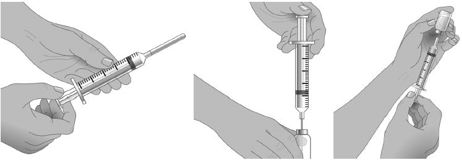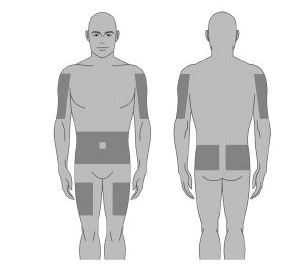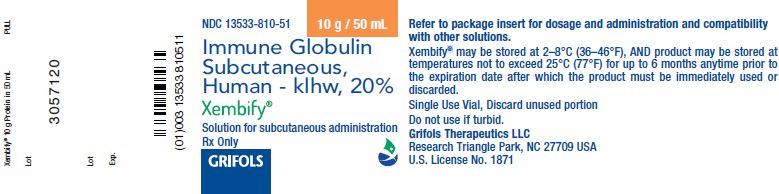 DRUG LABEL: XEMBIFY
NDC: 13533-810 | Form: SOLUTION
Manufacturer: GRIFOLS USA, LLC
Category: other | Type: PLASMA DERIVATIVE
Date: 20250317

ACTIVE INGREDIENTS: Human Immunoglobulin G 200 mg/1 mL
INACTIVE INGREDIENTS: Glycine; Polysorbate 80; Water

HIGHLIGHTS OF PRESCRIBING INFORMATION

These highlights do not include all the information needed to use XEMBIFY safely and effectively. See full prescribing information for XEMBIFY.
XEMBIFY (immune globulin subcutaneous, human – klhw) 20% solution
Initial U.S. Approval: 2019

WARNING: THROMBOSIS

See full prescribing information for complete boxed warning.

- Thrombosis may occur with immune globulin products, including XEMBIFY. Risk factors may include: advanced age, prolonged immobilization, hypercoagulable conditions, history of venous or arterial thrombosis, use of estrogens, indwelling vascular catheters, hyperviscosity, and cardiovascular risk factors. Thrombosis may occur in the absence of known risk factors.
- For patients at risk of thrombosis, administer XEMBIFY at the minimum dose and infusion rate practicable. Ensure adequate hydration in patients before administration. Monitor for signs and symptoms of thrombosis and assess blood viscosity in patients at risk for hyperviscosity.

1 INDICATIONS AND USAGE

XEMBIFY® (immune globulin subcutaneous, human-klhw) is a 20% immune globulin solution for subcutaneous injection indicated for treatment of Primary Humoral Immunodeficiency (PI) in patients 2 years of age and older. (1)

RECENT MAJOR CHANGES

Dosage and Administration, Dose (2.1) 7/2024
Dosage and Administration, Administration (2.3) 7/2024

2 DOSAGE AND ADMINISTRATION

For subcutaneous infusion only
Dose (2.1)
XEMBIFY can be administered at regular intervals from daily up to every two weeks (biweekly).

- Switching to XEMBIFY from intravenous immune globulin (IVIG): If a patient is switching to XEMBIFY, obtain the patient’s serum IgG trough level to guide subsequent dose adjustments.
  Establish the initial weekly dose in grams by converting the monthly (or every 3 weeks) IVIG dose into an equivalent weekly dose and increasing it by using a dose adjustment factor (1.37)
  Initial weekly = Prior IVIG dose (in grams) × 1.37
  dose (grams) Number of weeks between IVIG doses
  - Weekly: Begin XEMBIFY one week after last IVIG infusion.
  - Frequent dosing (2-7 times per week): Divide the calculated weekly dose by the desired number of times per week.
  - Biweekly dosing (every 2 weeks): Multiply the weekly dose by 2.
- Switching to XEMBIFY from subcutaneous immune globulin (IGSC): Administer the same weekly dose (grams) as the weekly dose of prior IGSC treatment (grams).
- Treatment-naïve patients: For patients starting IgG replacement (not switching from IVIG or IGSC) administer loading doses of 150 mg/kg/day for 5 consecutive days, followed by weekly administrations starting at Day 8 at 150 mg/kg/week. Monitor IgG trough levels frequently every 2 weeks during first 8 weeks.

Administration (2.3)
Infusion sites: up to 6 infusion sites simultaneously, with at least 2 inches (5 cm) between sites avoiding bony prominences, visible blood vessels, scars, and any areas of inflammation (irritation) or infection. Rotate sites for each administration.

Patient Age | Maximum Volume (mL/infusion site) | Infusion Rate (mL/hr/infusion site)
Children 2 to <10 years | 25 | ≤25
Adults, children ≥10 years | 25 | ≤35

3 DOSAGE FORMS AND STRENGTHS

XEMBIFY is a solution containing 0.2 g/mL (200 mg/mL; 20%) protein solution for subcutaneous infusion. (3)

4 CONTRAINDICATIONS

- Anaphylactic or severe systemic reactions to human immunoglobulin or inactive ingredients of XEMBIFY such as polysorbate 80. (4)
- IgA deficient patients with antibodies against IgA and a history of hypersensitivity. (4)

5 WARNINGS AND PRECAUTIONS

- Aseptic Meningitis Syndrome (AMS) occurs within two days of treatment. (5.1)
- Hypersensitivity and anaphylactic reactions may occur. IgA deficient patients with antibodies against IgA are at greater risk of developing severe hypersensitivity or anaphylactic reactions. (5.3)
- Monitor for renal function in patients at risk for renal failure. (5.4)
- Hemolysis can develop. Risk factors include high doses and non-O blood group. Closely monitor for hemolysis and hemolytic anemia. (5.5)
- Monitor patients for pulmonary adverse reactions (transfusion-related acute lung injury [TRALI]). (5.6)
- XEMBIFY is made from human plasma and may carry a risk of transmitting infectious agents, e.g., viruses, the variant Creutzfeldt-Jakob disease (vCJD) agent and, theoretically, the Creutzfeldt-Jakob disease (CJD) agent. (5.7)
- Passive transfer of antibodies may confound serologic testing. (5.8)

6 ADVERSE REACTIONS

The most common adverse reactions in ≥ 5% of patients in the clinical trial were local adverse reactions including infusion site erythema (redness), infusion site pain, infusion site swelling (puffiness), infusion site bruising, infusion site nodule, infusion site pruritus (itching), infusion site induration (firmness), infusion site scab, infusion site edema, and systemic reactions including cough and diarrhea. (6.1)
To report SUSPECTED ADVERSE REACTIONS, contact Grifols Therapeutics LLC at 1-800-520-2807 or FDA at 1-800-FDA-1088 or www.fda.gov/medwatch.

7 DRUG INTERACTIONS

The passive transfer of antibodies may transiently interfere with the response to live virus vaccines, such as measles, mumps, rubella, and varicella. (7.2)

8 USE IN SPECIFIC POPULATIONS

Geriatric: In patients over 65 years, do not exceed the recommended dose and infuse XEMBIFY at the minimum rate practicable. (8.5)

FULL PRESCRIBING INFORMATION

WARNING: THROMBOSIS

- Thrombosis may occur with immune globulin products, including XEMBIFY. Risk factors may include: advanced age, prolonged immobilization, hypercoagulable conditions, history of venous or arterial thrombosis, use of estrogens, indwelling central vascular catheters, hyperviscosity, and cardiovascular risk factors. Thrombosis may occur in the absence of known risk factors. [see Warnings and Precautions (5.2), Patient Counseling Information (17)]
- For patients at risk of thrombosis, administer XEMBIFY at the minimum dose and infusion rate practicable. Ensure adequate hydration in patients before administration. Monitor for signs and symptoms of thrombosis and assess blood viscosity in patients at risk for hyperviscosity. [see Warnings and Precautions (5.2)]

1 INDICATIONS AND USAGE

XEMBIFY® (immune globulin subcutaneous, human–klhw) is a 20% immune globulin solution for subcutaneous injection indicated for treatment of primary humoral immunodeficiency (PI) in patients 2 years of age and older. This includes, but is not limited to, congenital agammaglobulinemia, common variable immunodeficiency, X-linked agammaglobulinemia, Wiskott-Aldrich syndrome, and severe combined immunodeficiencies.^1-4

2 DOSAGE AND ADMINISTRATION

For subcutaneous infusion only

2.1 Dose

XEMBIFY can be administered at regular intervals from daily up to every two weeks (biweekly).
Doses divided over the course of a week, once weekly, or biweekly achieve similar exposure when administered regularly at steady-state.
Individualize the dose based on the patient’s pharmacokinetic and clinical response.
Monitor serum IgG trough levels regularly to guide subsequent dose adjustments and dosing intervals as needed (see Dose adjustments).

If a patient is switching to XEMBIFY, obtain the patient’s serum IgG trough level to guide subsequent dose adjustments.
Switching to XEMBIFY from intravenous immune globulin (IVIG) Begin treatment with XEMBIFY one week after the patient’s last IVIG infusion.
Calculate the initial weekly dose of XEMBIFY. Divide the previous monthly (or every 3 weeks) IVIG dose in grams by the number of weeks between IVIG infusions, then multiply this dose by the dose adjustment factor of 1.37.

Initial weekly dose (grams) = | Prior IVIG dose (in grams) | x 1.37
Initial weekly dose (grams) = | Number of weeks between IVIG doses | x 1.37

To convert the XEMBIFY dose (in grams) to milliliters (mL), multiply the calculated Initial SC dose (in grams) by 5.
To determine the dose for alternative regular dosing intervals:
-Frequent dosing (2-7 times per week): Divide the calculated weekly dose by the desired number of times per week.
-Biweekly dosing: Multiply the calculated weekly dose by 2.
To guide dose adjustments, see section Dose adjustments (Table 2).
Switching to XEMBIFY from subcutaneous immune globulin (IGSC)
Administer the same weekly dose of XEMBIFY (in grams) as the weekly dose of prior IGSC treatment (in grams).
To convert the XEMBIFY dose (in grams) to milliliters (mL), multiply the calculated Initial SC dose (in grams) by 5.
To determine the dose for alternative regular dosing intervals:
-Frequent dosing (2-7 times per week): Divide the calculated weekly dose by the desired number of times per week.
-Biweekly dosing: Multiply the calculated weekly dose by 2.
To guide dose adjustments, see section Dose adjustments (Table 2).
Treatment-naïve patients
The recommended dosage for treatment naïve patients with Primary Immunodeficiency is shown in Table 1.

Table 1: Dosing Regimen for Treatment-naïve Patients with Primary Immunodeficiency
Loading Dose | Maintenance Dose | IgG Trough Monitoring
150 mg/kg/day for 5 consecutive days | 150 mg/kg/week - weekly administrations starts at Day 8 | Monitor IgG trough levels every 2 weeks for the first 8 weeks of XEMBIFY dosing

To guide dose adjustments, see section Dose adjustments (Table 2).
Dose adjustments
For dose adjustments, calculate the difference (in mg/dL) of the patient’s serum IgG trough level from the target IgG trough level, then find this difference in Table 2 (below). Locate the corresponding amount (in mL) by which to increase or decrease the weekly dose based on the patient’s body weight. For example, if a patient with a body weight of 70 kg has an actual IgG trough level of 900 mg/dL and the target level is 1,000 mg/dL, this results in a difference of 100 mg/dL. Therefore, increase the weekly dose of subcutaneous dose by 5 mL.
The patient’s clinical response should be the primary consideration in dose adjustment. If a patient on XEMBIFY does not maintain an adequate clinical response or a serum IgG trough level equivalent to that of a previous treatment, adjust the dose accordingly.

Table 2: Adjustment (±mL) of the Weekly Subcutaneous Dose Based on the Difference (±mg/dL) From the Target Serum IgG Trough Level
Difference From Target IgG Trough Level (mg/dL) | Body Weight (kg)
Difference From Target IgG Trough Level (mg/dL) | 10 | 15 | 20 | 30 | 40 | 50 | 60 | 70 | 80 | 90 | 100 | 110 | 120
Difference From Target IgG Trough Level (mg/dL) | Dose Adjustment (mL per Week) [Dose adjustment in mL is based on the slope of the serum IgG trough level response to subcutaneous administration of XEMBIFY dose increments (about 6.6 mg/dL per increment of 1 mg/kg per week).]
50 | 0 | 1 | 1 | 1 | 2 | 2 | 2 | 3 | 3 | 3 | 4 | 4 | 5
100 | 1 | 1 | 2 | 2 | 3 | 4 | 5 | 5 | 6 | 7 | 8 | 8 | 9
150 | 1 | 2 | 2 | 3 | 5 | 6 | 7 | 8 | 9 | 10 | 11 | 13 | 14
200 | 2 | 2 | 3 | 5 | 6 | 8 | 9 | 11 | 12 | 14 | 15 | 17 | 18
250 | 2 | 3 | 4 | 6 | 8 | 9 | 11 | 13 | 15 | 17 | 19 | 21 | 23
300 | 2 | 3 | 5 | 7 | 9 | 11 | 14 | 16 | 18 | 20 | 23 | 25 | 27
350 | 3 | 4 | 5 | 8 | 11 | 13 | 16 | 19 | 21 | 24 | 27 | 29 | 32
400 | 3 | 5 | 6 | 9 | 12 | 15 | 18 | 21 | 24 | 27 | 30 | 33 | 36
450 | 3 | 5 | 7 | 10 | 14 | 17 | 20 | 24 | 27 | 31 | 34 | 38 | 41
500 | 4 | 6 | 8 | 11 | 15 | 19 | 23 | 27 | 30 | 34 | 38 | 42 | 45

2.2 Preparation and Handling

XEMBIFY is a clear to slightly opalescent, and colorless or pale yellow solution.

Visually inspect XEMBIFY for particulate matter and discoloration prior to administration, whenever solution and container permit.

Do not use if the solution is cloudy or turbid.

Do not shake.

Do not dilute.

The XEMBIFY vial is for single use only.

Do not store any vial that has been entered by a needle during preparation for infusion, punctured, partially used, or opened.

Administer within 8 hours after beginning infusion preparation (i.e., once XEMBIFY is transferred from the vial into a syringe).

Administer XEMBIFY separately from other drugs or medications that the patient may be receiving.

Do not mix XEMBIFY with other medications including immune globulins from other manufacturers.

Do not use after expiration date.

Discard unused portion.

2.3 Administration

Prior to use, allow the solution to reach ambient room temperature.
Do not shake.
Follow the steps below and use aseptic technique to administer XEMBIFY.

1. Inspect the vials: inspect for clarity, color, and expiration date (s).
2. Prepare for infusion:
Gather supplies: XEMBIFY vial(s), ancillary supplies, sharps container, patient’s
treatment diary/logbook, and the infusion pump.
Prepare a clean work area.
Wash hands.
3. Remove the protective cap from the vial to expose the central portion of the stopper.
If the packaging shows any sign of tampering, do not use the product and notify
Grifols Therapeutics LLC immediately [1-800-520-2807].
4. Wipe the stopper with alcohol and allow to dry.

5. Using a sterile syringe and needle, prepare to withdraw XEMBIFY by first injecting air into the vial that is equivalent to the amount of XEMBIFY to be withdrawn. Then withdraw the desired volume of XEMBIFY. If multiple vials are required to achieve the desired dose, repeat this step. (Figure 1)
6. Use XEMBIFY as soon as practicable, within 2 hours to avoid the potential formation of particles caused by siliconized syringes.

7. Follow the manufacturer’s instructions for preparing the pump and administration tubing. Be sure to prime the administration tubing to ensure that no air is left in the tubing or needle by filling the tubing/needle with XEMBIFY.

8. Select the number and location of injection sites. Rotate sites for each administration. (Figure 2)
  Infuse XEMBIFY in the abdomen, thigh, upper arm, sides, back and/or lateral hip.
  Avoid bony areas, scars, areas of inflammation, superficial infection or blood vessels.

9. Cleanse the injection site(s) with antiseptic solution using a circular motion working from the center of the site and moving to the outside. Sites should be clean, dry, and at least 2 inches (5 cm) apart. (Figure 3)

10. Grasp the skin between 2 fingers (pinch at least one inch (2.5 cm) of skin) and insert the needle at a 90-degree angle into the subcutaneous tissue. (Figure 4)

11. After inserting each needle, make sure that a blood vessel has not been accidentally entered. Attach a sterile syringe to the end of the primed administration tubing, pull back on the plunger, and if you see blood, remove and discard the needle and administration tubing. (Figure 5)

12. Repeat priming and needle insertion steps using a new needle, administration tubing
and a new infusion site. Secure the needle in place by applying sterile gauze or
transparent dressing over the site.

13. Infuse XEMBIFY at a maximum rate as per Table 3 using up to 6 infusion sites. Ensure
that the infusion sites are at least 2 inches (5 cm) apart for patients of all ages. The
number of infusion sites is at healthcare provider discretion. Children will require less
total volume for a specific XEMBIFY dose (mg/kg body weight) than adults. The
healthcare provider may choose a smaller volume/site for children and/or fewer infusion
sites to achieve the target total dose, depending on the needs of the child. The total dose
volume of XEMBIFY is divided by the desired volume (mL/site) to obtain number
of infusion sites to be used.

Table 3: Infusion Parameters for Children and Adults with PI
Patient Age | Maximum Volume to Be Infused SC | Rate | Number of Infusion Sites | Site Distance Apart
Children 2 to <10 years of age | 25 mL per site | ≤25 mL/hr/infusion site | ≤6 | ≥2 inches (5 cm)
Adults and children 10 years and older | 25 mL per site | ≤35 mL/hr/infusion site | ≤6 | ≥2 inches (5 cm)

Record information about the infusion (e.g., lot number, expiration date, dose, date,
time, infusion site location(s), side effects) in a patient treatment record or infusion
log.
14. Discard the needle(s) and infusion line(s) in an appropriate container. Follow the
manufacturer’s instructions for storage of the infusion pump.
15. Discard partially used vial(s).

3 DOSAGE FORMS AND STRENGTHS

XEMBIFY is a protein solution containing 20% IgG (200 mg/mL; 0.2 g/mL) for subcutaneous infusion.

4 CONTRAINDICATIONS

XEMBIFY is contraindicated in:

Patients who have had an anaphylactic or severe systemic reaction to the administration of human immune globulin.

IgA deficient patients with antibodies against IgA and history of hypersensitivity to human immune globulin treatment.

5 WARNINGS AND PRECAUTIONS

5.1 Aseptic Meningitis Syndrome

Aseptic meningitis syndrome (AMS) has been reported with the use of human immune globulin administered intravenously and subcutaneously, including XEMBIFY. AMS usually begins within several hours to 2 days following immune globulin treatment. AMS may occur more frequently in females than in males.

AMS is characterized by the following signs and symptoms: severe headache, nuchal rigidity, drowsiness, fever, photophobia, painful eye movements, nausea and vomiting. Cerebrospinal fluid (CSF) studies frequently show pleocytosis up to several thousand cells per cubic millimeter, predominantly from the granulocytic series, and elevated protein levels up to several hundred mg/dL, but negative culture results. To rule out other causes of meningitis, conduct a thorough neurological examination on patients exhibiting such symptoms and signs, including CSF studies. AMS may occur more frequently in association with high doses (>2 g/kg) and/or rapid infusion of immune globulin products. Discontinuation of immune globulin treatment has resulted in remission of AMS within several days without sequelae.

5.2 Thrombosis

Thrombosis may occur following treatment with immune globulin products, including XEMBIFY.^5-7 Risk factors may include advanced age, prolonged immobilization, hypercoagulable conditions, history of venous or arterial thrombosis, use of estrogens, indwelling central vascular catheters, hyperviscosity, and cardiovascular risk factors. Thrombosis may occur in the absence of known risk factors.

Consider baseline assessment of blood viscosity in patients at risk for hyperviscosity, including those with cryoglobulins, fasting chylomicronemia/markedly high triacylglycerols (triglycerides), or monoclonal gammopathies. For patients at risk of thrombosis, administer XEMBIFY at the minimum dose and infusion rate practicable. Ensure adequate hydration in patients before administration. Monitor for signs and symptoms of thrombosis and assess blood viscosity in patients at risk for hyperviscosity. [see Boxed Warning, Dosage and Administration (2.3), Patient Counseling Information (17)]

5.3 Hypersensitivity

Severe hypersensitivity reactions may occur with human immune globulin products, including XEMBIFY. If a hypersensitivity reaction occurs, discontinue the XEMBIFY infusion immediately and institute appropriate treatment.

XEMBIFY contains IgA. Patients with known anti-IgA antibodies have a greater risk of developing potentially severe hypersensitivity reactions, including anaphylaxis. XEMBIFY is contraindicated in IgA deficient patients with antibodies against IgA and history of hypersensitivity to human immune globulin treatment. [see Contraindications (4)]

5.4 Renal Dysfunction/Failure

Acute renal dysfunction/failure, acute tubular necrosis, proximal tubular nephropathy, osmotic nephrosis and death may occur upon use of human immune globulin products, especially those containing sucrose.^8,9 XEMBIFY does not contain sucrose. Ensure that patients are not volume depleted prior to administration of XEMBIFY.

In patients with any degree of preexisting renal insufficiency or predisposition to acute renal failure (such as diabetes mellitus, age greater than 65 years, volume depletion, sepsis, paraproteinemia, or patients receiving known nephrotoxic drugs), monitor renal function and consider lower, more frequent dosing. [see Dosage and Administration (2.3)]

Periodic monitoring of renal function and urine output is particularly important in patients judged to have a potential increased risk for developing acute renal failure. Assess renal function, including measurement of blood urea nitrogen (BUN)/serum creatinine, prior to the initial infusion of XEMBIFY and again at appropriate intervals thereafter. If renal function deteriorates, consider discontinuation of XEMBIFY. [see Patient Counseling Information (17)]

5.5 Hemolysis

IgG products, including XEMBIFY can contain blood group antibodies that may act as hemolysins and induce in vivo coating of red blood cells (RBCs) with immunoglobulin, causing a positive direct antiglobulin (Coombs’) test result and hemolysis.^10-13 Delayed hemolytic anemia can develop subsequent to human immune globulin therapy due to enhanced RBC sequestration, and acute hemolysis consistent with intravascular hemolysis has been reported. [see Adverse Reactions (6)]

Monitor XEMBIFY recipients for clinical signs and symptoms of hemolysis, particularly patients with risk factors such as non-O blood group, or patients receiving high IgG doses (≥ 2 grams/kg).^14 Underlying inflammatory state in an individual patient may increase the risk of hemolysis, but its role is uncertain.^15

If signs and/or symptoms of hemolysis are present after XEMBIFY infusion, perform appropriate confirmatory laboratory testing.

5.6 Transfusion-Related Acute Lung Injury

Noncardiogenic pulmonary edema (transfusion-related acute lung injury [TRALI]) may occur in patients following treatment with human immune globulin products.^16 TRALI is characterized by severe respiratory distress, pulmonary edema, hypoxemia, normal left ventricular function, and fever. Symptoms typically occur within 1 to 6 hours after treatment.

Monitor patients for pulmonary adverse reactions. If TRALI is suspected, perform appropriate tests for the presence of anti-neutrophil and anti-HLA antibodies in both the product and patient serum. TRALI may be managed using oxygen therapy with adequate ventilatory support.

5.7 Transmissible Infectious Agents

Because XEMBIFY is made from human blood, it may carry a risk of transmitting infectious agents, e.g., viruses, the variant Creutzfeldt-Jakob disease (vCJD) agent and, theoretically, the Creutzfeldt-Jakob disease (CJD) agent. This also applies to unknown or emerging viruses and other pathogens. No cases of transmission of viral diseases or CJD have been associated with the use of XEMBIFY. ALL infections suspected by a physician to have possibly been transmitted by XEMBIFY should be reported by the physician or other healthcare provider to Grifols Therapeutics LLC [1-800-520-2807].

5.8 Interference with Laboratory Tests

After infusion with XEMBIFY, the transitory rise of various passively transferred antibodies in the patient’s blood may yield false-positive serological testing results, with the potential for misleading interpretation. Passive transmission of antibodies to erythrocyte antigens (e.g., A, B, and D) may cause a positive direct or indirect antiglobulin (Coombs’) test.

6 ADVERSE REACTIONS

6.1 Clinical Trials Experience

Because clinical studies are conducted under widely varying conditions, adverse reaction rates observed in the clinical trials of one drug cannot be directly compared to rates in other clinical trials of another drug and may not reflect the rates observed in clinical practice.
Study 1
The safety of XEMBIFY was evaluated in an open-label, single-arm prospective multi-center study in North America in patients with PI who received subcutaneous XEMBIFY for at least 6 months [see Clinical Studies (14)].

A total of 49 patients (including 14 patients between 2 to 16 years of age) received 1053 XEMBIFY infusions during the clinical trial. The average number of infusions per patient was 21.5 infusions, median 24 infusions (range 1-26 infusions).

A total of 390 local infusion site reactions occurred at a rate per infusion of 0.370 (approximately 1 in 2.7 infusions). Of these, the most common was infusion site erythema which had a median duration of 24.9 hours. Infusion site swelling, and infusion site pain had median durations of 24.5 and 22.8 hours, respectively. Local infusion site reactions of all kinds by site of infusion (where site of infusion was recorded) occurred in 50.0% and 52.6% of patients during infusions in the abdomen versus thigh, respectively, and across 773 abdominal infusions and 279 thigh infusions rates were 0.184 and 0.735 per infusion, respectively; this corresponds to 1 in 5.4 infusions (for abdomen) and 1 in 1.4 infusions (for thigh). No local infusion site reactions were considered severe or serious.

The adverse reactions occurring in ≥ 5% of patients on XEMBIFY in the clinical trial for the duration of the subcutaneous (SC) phase are shown in Table 4 below which includes all treatment-emergent adverse reactions except infections.

Table 4: Adverse Reactions in ≥ 5% of Patients During Treatment [The term ‘treatment’ refers to the duration of the subcutaneous phase of XEMBIFY administration.] with XEMBIFY in Study 1
Adverse Reaction [Including all adverse reactions that occurred after the first dose of XEMBIFY regardless of causality, excluding infections.] | By Patient n (%) [Number and percentage of patients with the adverse reaction.] (N=49 patients) | By Infusion n (rate) [Rate per infusion is calculated as the total number of adverse reactions divided by the total number of infusions.] (N=1053 infusions)
Infusion site erythema | 19 (39%) | 123 (<1)
Infusion site pain | 9 (18%) | 32 (<1)
Infusion site swelling | 8 (16%) | 124 (<1)
Infusion site bruising | 8 (16%) | 26 (<1)
Infusion site nodule | 8 (16%) | 13 (<1)
Infusion site pruritus | 5 (10%) | 28 (<1)
Infusion site induration | 4 (8%) | 6 (<1)
Infusion site scab | 3 (6%) | 6 (<1)
Infusion site edema | 3 (6%) | 5 (<1)
Cough | 3 (6%) | 4 (<1)
Diarrhea | 3 (6%) | 3 (<1)

Four patients discontinued XEMBIFY due to adverse reactions which were infusion site nodules, infusion site discomfort, skin papules/plaques, and arthralgia/myalgia.

Study 2

The safety of XEMBIFY during 12 months of treatment was evaluated in 61 patients (including 29 pediatric patients aged 2 to ≤16 years) in a clinical trial in Europe [see Clinical Studies (14)]. Adverse reactions in pediatric and adult patients were similar to those observed in Study 1. Among early withdrawals from the study, one patient discontinued XEMBIFY due to a related infusion site fibroma that resolved.

Study 3

The safety of XEMBIFY was compared between weekly and biweekly dosing during a single-sequence weekly-to-biweekly crossover study of 27 treatment-experienced adult patients with PI [see Clinical Studies (14)]. The incidence of adverse reactions was similar between dosing regimens and similar to those observed in Study 1.

The safety of XEMBIFY administered to 6 treatment-naïve adults with PI was assessed during a loading dose phase of 5 daily treatments with XEMBIFY followed by a weekly maintenance phase [see Clinical Studies (14)]. Adverse reactions occurring in more than one patient included infusion site swelling in 2 (33%) patients during or after 13 infusions and infusion site bruising in 2 (33%) patients during or after 2 infusions.

6.2 Postmarketing Experience

The following adverse events have been identified during post approval use of XEMBIFY. Because these events are reported voluntarily and from a population of uncertain size, it is not always possible to reliably estimate the frequency of these events or establish a causal relationship to product exposure.

Immune system disorders: Anaphylactic reaction and hypersensitivity

Nervous system disorders: Aseptic meningitis, dizziness, and paresthesia

Cardiovascular disorders: Tachycardia and hypotension

Respiratory, thoracic and mediastinal disorders: Dyspnea and chest discomfort

General disorders and administration site conditions: Injection site reactions (such as
induration and warmth), chills, fatigue, and pain

The following adverse events have been identified and reported during the postmarketing use of immune globulin products administered subcutaneously:

Nervous system disorders: Tremor

Respiratory, thoracic and mediastinal disorders: Laryngospasm

7 DRUG INTERACTIONS

7.1 Serological Testing

Various passively transferred antibodies in immunoglobulin preparations, including XEMBIFY, can confound the results of serological testing.

7.2 Live Attenuated Virus Vaccines

Passive transfer of antibodies may transiently interfere with the immune response to live virus vaccines such as measles, mumps, rubella and varicella. Inform the immunizing healthcare provider of recent therapy with XEMBIFY so that appropriate measures may be taken.

8 USE IN SPECIFIC POPULATIONS

8.1 Pregnancy

Risk Summary

No human data are available to indicate the presence or absence of drug associated risk. Animal reproduction studies have not been conducted with XEMBIFY. It is not known whether XEMBIFY can cause fetal harm when administered to a pregnant woman or can affect reproduction capacity. Immune globulins cross the placenta from maternal circulation increasingly after 30 weeks of gestation. XEMBIFY should be given to a pregnant woman only if clearly indicated. In the U.S. general population, the estimated background risk of major birth defect and miscarriage in clinically recognized pregnancies is 2-4% and 15-20%, respectively.

8.2 Lactation

Risk Summary

No human data are available to indicate the presence or absence of drug associated risk. The developmental and health benefits of breastfeeding should be considered along with the mother’s clinical need for XEMBIFY and any potential adverse effects on the breastfed infant from XEMBIFY or from the underlying maternal condition.

8.4 Pediatric Use

XEMBIFY was evaluated in 14 pediatric patients (2-16 years of age) with PI in a multi-center clinical trial (Study 1) and in 29 pediatric patients in Study 2 [see Clinical Studies (14)]. The safety and efficacy profiles were similar to adult patients. No pediatric-specific dose requirements were necessary to achieve the desired serum IgG levels.

The safety and effectiveness of XEMBIFY in pediatric patients below 2 years of age have not been established.

8.5 Geriatric Use

Clinical studies of XEMBIFY did not include sufficient numbers of patients over age 65 years to determine whether they respond differently from younger patients. In general, dose selection for an elderly patient should be cautious, usually starting at the low end of the dosing range, reflecting the greater frequency of decreased hepatic, renal, or cardiac function, and of concomitant disease or other drug therapy.

11 DESCRIPTION

XEMBIFY, immune globulin subcutaneous, human-klhw, is a 20% ready-to-use sterile, non-pyrogenic solution of human immune globulin protein for subcutaneous administration. The purity is ≥ 98% IgG with a sub-class distribution similar to that found in normal serum.

XEMBIFY consists of 18% to 22% protein in 0.16 M to 0.26 M glycine and 10 to 40 mcg/ mL polysorbate 80 at a pH of 4.1 to 4.8. The solution is clear to slightly opalescent, and colorless or pale yellow. The osmolality range is 280 to 404 mOsmol/kg. XEMBIFY contains no preservative and is not made with natural rubber latex.

XEMBIFY is made from large pools of human plasma by a combination of cold ethanol fractionation, caprylate precipitation and filtration, and anion-exchange chromatography. Isotonicity is achieved by the addition of glycine. XEMBIFY is incubated in the final container (at the low pH of 4.1 to 4.8).

The capacity of the manufacturing process to remove and/or inactivate enveloped and non-enveloped viruses has been validated by laboratory spiking studies on a scaled down process model, using the following enveloped and non-enveloped viruses: human immunodeficiency virus, type I (HIV-1) as the relevant virus for HIV-1 and HIV-2; bovine viral diarrhea virus (BVDV) as a model for hepatitis C virus; pseudorabies virus (PRV) as a model for large enveloped DNA viruses (e.g. herpes viruses); West Nile Virus (WNV) as a relevant virus; Reovirus type 3 (Reo) as a model for non-enveloped viruses and for its resistance to physical and chemical inactivation; hepatitis A virus (HAV) as relevant non-enveloped virus, and porcine parvovirus (PPV) as a model for human parvovirus B19.

Overall virus clearance capacity was calculated only from steps that were mechanistically independent from each other and truly additive. In addition, each step was verified to provide robust virus reduction across the production range for key parameters.

Table 5: Summary of Virus Clearance Capacity (Log10)
Process Step | Enveloped Virus |  |  |  | Non-Enveloped Virus
Process Step | HIV-1 | BVDV | PRV | WNV | Reo3 | HAV | PPV
Caprylate Precipitation/Depth Filtration | C/I [C/I: Interference by caprylate precluded determination of virus clearance capacity for this step.] | 2.7 | C/I | C/I | ≥3.5 | ≥3.6 | 4.0
Caprylate Incubation [DHBV and SINV were also evaluated for the caprylate incubation step. The log10 clearance capacities were ≥3.6 and ≥6.0, respectively.] | ≥4.5 | ≥4.5 | ≥4.6 | ≥5.1 | NA [NA = Not applicable: This step is not applicable to non-enveloped viruses.] | NA | NA
Column Chromatography | ≥3.0 | 4.0 | ≥3.3 | ND [Due to interfering effects of the process intermediate matrix the virus clearance capacity could not be determined.] | ≥4.0 | ≥1.4 | 4.2
Nanofiltration | ≥3.7 | ≥4.1 | ND | ND | ≥1.8 | ND | 0.5
Low pH Final Container Incubation | ≥5.3 | 4.9 | ≥5.1 | ≥5.3 | NA | NA | NA
Overall Clearance Capacity | ≥16.5 | ≥20.2 | ≥13.0 | ≥10.4 | ≥9.3 | ≥5.0 | 8.2

Additionally, the manufacturing process was investigated for its capacity to decrease the infectivity of an experimental agent of transmissible spongiform encephalopathy (TSE), considered as a model for the variant Creutzfeldt-Jakob disease (vCJD), and Creutzfeldt-Jakob disease (CJD) agents.

Several of the individual production steps of the manufacturing process have been shown to decrease TSE infectivity of an experimental model agent. TSE reduction steps include depth filtrations (a total of ≥ 6.6 log10). These studies provide reasonable assurance that low levels of vCJD/CJD agent infectivity, if present in the starting material, would be removed.

12 CLINICAL PHARMACOLOGY

12.1 Mechanism of Action

XEMBIFY supplies a broad spectrum of opsonizing and neutralizing immunoglobulin G (IgG) antibodies against bacterial, viral, parasitic, and mycoplasmal agents and their toxins. XEMBIFY also contains a spectrum of antibodies capable of interacting with and altering the activity of cells of the immune system. The role of these antibodies and the mechanism of action of XEMBIFY are not fully understood.

12.2 Pharmacodynamics

Human normal immunoglobulin contains mainly (IgG) with a broad spectrum of antibodies against infectious agents. Human normal immunoglobulin contains the IgG antibodies present in the normal population. XEMBIFY has a distribution of IgG subclasses closely proportional to that in native human plasma. Adequate doses of XEMBIFY may restore abnormally low IgG levels to the normal range.

12.3 Pharmacokinetics

Pharmacokinetic (PK) parameters of subcutaneously administered XEMBIFY were evaluated in patients with primary immunodeficiency (PI) during a clinical trial in North America. [see Clinical Studies (14)] Patients were treated intravenously with a comparator product [GAMUNEX®-C, immune globulin injection (human), 10% caprylate/chromatography purified] during a 3-4 months run-in period prior to IV PK profiling in 50 patients, and then 49 patients switched to weekly subcutaneous infusions of XEMBIFY for 24 weeks at 137% of the intravenous dose with PK profiling at SC Week #13-14. A comparison of the area under the curve (AUC) for subcutaneous versus intravenous infusion was performed.

At the 137% dose adjustment, the geometric least-squares means ratio of the AUC for subcutaneous XEMBIFY versus IV administration of GAMUNEX-C was 104% (90% CI: 100%-107%). The peak IgG level occurred at a mean of 76 hours after subcutaneous XEMBIFY administration. The average mean IgG trough level at steady state was higher with XEMBIFY (1245 mg/dL) compared with IV GAMUNEX-C (957 mg/dL) (average mean trough ratio SC/IV of 1.3). PK parameters of XEMBIFY compared to IV GAMUNEX-C are summarized in Table 6. PK parameters did not significantly differ between age groups (Table 7).

Table 6: PK Parameters of Total IgG at Steady-State in IV and SC Phases (PK Population) in Children and Adults
Phase | Statistics | AUC(0-7 days) (h*mg/dL) [AUC(0-7 days) in the IV Phase is calculated as AUC(0-21 days)/3 for patients on an every-3-week IV dosing schedule (n=6), and as AUC(0-28 days)/4 for patients on an every-4-week IV dosing schedule (n=43).] | Cmax (mg/dL) | tmax (hour)
IV | N | 49 | 49 | 49
IV | Mean±SD | 212151±41832 | 2154±437 | 5.8±8.0
IV | CV% | 20 | 20 | 137.9
IV | Min, Max | 106091, 308405 | 1430, 3170 | 0.8, 48.9
SC | N | 39 | 41 | 41
SC | Mean±SD | 218316±48121 | 1395±312 | 76.1±35.7
SC | CV% | 22 | 22 | 46.9
SC | Min, Max | 102650, 367496 | 636, 2320 | 0.0, 167.7 [The apparent variability in tmax in the SC Phase can be attributed to the low fluctuation in IgG concentrations and is unlikely to be of any clinical relevance.]

Table 7: Steady-State PK Parameters for XEMBIFY by Age
Age Group (years) Statistics | AUC(0-7 days) (h*mg/dL) | Cmax (mg/dL) | Mean Trough (mg/dL) | tmax (hour)
2 -5 (n) | 1 | 1 | 1 | 1
Mean±SD | 183864±NC [NC = Not calculated] | 1130±NC | 1078±NC | 72±NC
>5 -12 (n) | 5 | 5 | 6 | 5
Mean±SD | 215558±27604 | 1372±183 | 1194±183 | 71±26
CV% | 13 | 13 | 15 | 37
Min, Max | 187838, 245614 | 1200, 1580 | 993, 1510 | 28, 101
>12 -16 (n) | 4 | 5 | 5 | 5
Mean±SD | 240009±40578 | 1548±281 | 1379±209 | 73±50
CV% | 17 | 18 | 15 | 68
Min, Max | 205646, 298678 | 1290, 2000 | 1095, 1665 | 24, 143
>16 (n) | 29 | 30 | 32 | 30
Mean±SD | 216987±52389 | 1383±335 | 1239±296 | 78±36
CV% | 24 | 24 | 24 | 47
Min, Max | 102650, 367496 | 636, 2320 | 652, 2048 | 0, 168

A study evaluating serial PK parameters between weekly and biweekly (every 2 weeks) dosing regimens for treatment-experienced adults with PI included 25 evaluable patients, including 23 who were evaluable for both dosing regimens. The geometric least-squares means ratio of the AUC(0-7 days) for XEMBIFY administration biweekly compared to weekly is 104% (90% CI: 100%-107%). PK parameters at steady state comparing weekly to biweekly dosing of XEMBIFY are summarized in Table 8. For biweekly dosing, population PK modeling demonstrates simulated steady state Cmax, Cmin, and AUCtau values of pediatric patients are within the 5th to 95th percentile of adult values.

Table 8: Steady State PK Parameters for XEMBIFY Weekly and Biweekly Dosing in Adult PK Population
Period | Statistics | AUC(0-7 days) (h*mg/dL) [AUC(0-7 days) in the biweekly period is calculated as AUC(0-14 days)/2 for patients on an every 2-week dosing schedule.] | Cmax (mg/dL) | tmax (hour)
Weekly | n | 23 | 25 | 25
Weekly | Mean±SD | 170386 ± 35949 | 1076 ± 228 | 79 ± 40
Biweekly | n | 23 | 23 | 23
Biweekly | Mean±SD | 174561 ± 36974 | 1151 ± 243 | 103 ± 44

A study in treatment-naïve adults with PI (n=6) evaluated the trough IgG levels following initiation of a XEMBIFY loading dose regimen (150 mg/kg/day for 5 consecutive days) and after weekly maintenance XEMBIFY dosing regimen (150 mg/kg/week for 32 weeks). Following the initial loading dose and prior to initiating maintenance dosing, five (83%) patients attained an IgG trough level >700 mg/dL at Week 1 (Day 8). Three (50%) patients required dose adjustments. All 6 patients attained IgG trough levels >700 mg/dL by Week 8 and were maintained through the end of the study at Week 32. During the weekly maintenance phase patients received 150 mg/kg/week - 180 mg/kg/week of XEMBIFY and had mean trough IgG levels of at least 901 mg/dL at all timepoints from Week 8 through the end of study Week 32. Simulated population PK analysis (including data from previously treated pediatric and adult patients with PI) showed similar IgG exposure to treatment naïve patients following a loading dose and maintenance dose regimen of XEMBIFY. The IgG exposure following a loading dose plus maintenance dose regimen is expected to be similar between treatment-naïve pediatric and adult patients.

13 NONCLINICAL TOXICOLOGY

13.1 Carcinogenesis, Mutagenesis, Impairment of Fertility

No nonclinical studies were conducted to evaluate the carcinogenic or mutagenic effects of XEMBIFY or its effects on fertility.

13.2 Animal Toxicology and/or Pharmacology

Single and repeated dose toxicology studies were conducted in male New Zealand White rabbits. In a single-dose toxicity study, no adverse effects were observed with subcutaneous dose levels of 500, 1000 and 1500 mg/kg. In a repeated-dose toxicity study, the systemic safety and toxicity profiles of XEMBIFY and comparator GAMUNEX-C were similar following 5 consecutive daily subcutaneous doses at levels of 500, 1000 and 1500 mg/kg/day. Transient local injection site swelling was observed in XEMBIFY but not in the GAMUNEX-C groups.

In improper delivery route studies, XEMBIFY administered as a single intravenous, intra-arterial or perivascular dose of 100 mg/kg caused injection site irritation in New Zealand White rabbits. The findings were of higher incidence following perivascular administration of either XEMBIFY or GAMUNEX-C and were within the norms of this route of administration in this species.

14 CLINICAL STUDIES

Study 1
Study 1 was a prospective, open-label single-arm, multi-center clinical trial designed to evaluate safety, efficacy, and pharmacokinetics of XEMBIFY in patients with PI conducted in North America. Safety and pharmacokinetics were assessed as compared to GAMUNEX-C. The GAMUNEX-C run-in phase prior to XEMBIFY (subcutaneous phase) lasted 3 or 4 months to achieve steady state prior to pharmacokinetic profiling. Efficacy was based on annualized serious bacterial infection (SBI) rate during the 6 months on XEMBIFY. The following were considered SBIs: bacteremia/sepsis, bacterial meningitis, bacterial pneumonia, osteomyelitis/septic arthritis, or visceral abscess.

A total of 53 adult and pediatric patients with PI enrolled (9% Hispanic or Latino; 91% White, 4% Black or African American, 6% American Indian or Alaskan Native). During the run-in and IV GAMUNEX-C phases, 4 patients discontinued. XEMBIFY was administered to a total of 49 patients (including 14 children aged 2 to ≤ 16 years and 35 adults) with a mean ± SD dose of 179 ± 45 mg/kg/week for a median treatment duration of 24 weeks and mean ± SD of 22 ± 7 weeks. The median dose was 171 mg/kg/week and the range of doses was 71 mg/kg/week to 276 mg/kg/week. The total exposure of XEMBIFY was 20 patient-years and 1053 infusions.

The rate of SBIs was 0.05 events per patient-year (1 event in 20 patient-years) (upper 99% confidence limit: 0.11) during XEMBIFY treatment. This annual rate was lower than 1.0 SBI/patient-year, the threshold specified as effective.

The summary of infections and associated events for patients during subcutaneous treatment with XEMBIFY in Study 1 is summarized in Table 9.

Table 9: Summary of Infections and Associated Events on XEMBIFY in Study 1
Parameters | Results
Number of patients (efficacy period) | 49
Total number of patient days on treatment | 7,407
Total number of patient-years on treatment | 20.28
Infections Annual rate of SBIs [Serious bacterial infections included bacteremia/sepsis, bacterial meningitis, bacterial pneumonia, osteomyelitis/septic arthritis, or visceral abscess.] (per patient-year) | 0.05 (95% CI: 0.02 - 0.10)
Annual rate of infections of any kind (per patient-year) | 2.4 (95% CI: 1.6 - 3.3)
Days on antibiotics (prophylactic) (rate per patient-year) | 27.7 (95% CI: 13.6 - 49.0)
Days on antibiotics (therapeutic) (rate per patient-year) | 28.9 (95% CI: 17.3 - 44.8)
Days missed work/school/unable to perform normal daily activities due to infections (rate per patient-year) | 2.3 (95% CI: 1.1 - 4.2)
Hospitalizations due to infections (rate per patient-year) | 0.05 (95% CI: 0.02 - 0.10)

Study 2
Study 2 was a prospective, open-label, single-arm, multi-center clinical trial designed to evaluate efficacy and safety of XEMBIFY conducted in the European Union and Australia in patients with PI. Efficacy was based on annualized SBI rate during 12 months on XEMBIFY using a 1:1 dose adjustment factor with the patient’s previous subcutaneous or IV IgG replacement regimen and a minimum XEMBIFY dose of 100 mg/kg/week. If the XEMBIFY infusion was well tolerated during 2 infusions with an initial target rate of less than or equal to 25 mL/hour/site, the infusion rate could be increased in a stepwise manner at the investigator’s discretion up to a maximum of 60 mL/hr/site, and if well tolerated, subsequent infusions could begin at that rate; the investigator could also decrease the infusion rate at any time based on the patient’s tolerability. The definition of SBI was the same as for Study 1.

Study 2 enrolled 61 patients with PI, including 32 adults and 29 children aged 2 to ≤ 16 years. The majority (93%) were White, and16% were Hispanic or Latino. During the study, 6 patients discontinued (including 4 due to adverse events). XEMBIFY was administered with a median dose of 113 mg/kg/week ranging 67 to 212 mg/kg/week. The median treatment duration was 52 weeks.

There was one SBI in a 10 year old patient for an annualized SBI rate of 0.017 events per patient-year (upper 99% confidence limit: 0.036) during XEMBIFY treatment. There were a total of 14 patients who were administered XEMBIFY SC infusions at rates greater than 25 mL/hr/site. Seven patients (6 male; 1 female) received at least 3 consecutive XEMBIFY SC infusions at rates of ≥35 mL/hr/site (4 children [ages 10-15 years] and 3 adults) and maximum infusion rates ranged from 38 mL/hr/site to 80 mL/hr/site. One patient discontinued from the study early while at a sustained infusion rate of 50 mL/hr/site due to an adverse reaction of subcutaneous fibroma (mild) that was initially reported while the patient was receiving XEMBIFY at a rate of 15 mL/hr/site. One patient (maximum infusion rate 38 mL/hr/site) experienced an adverse reaction of infusion site necrosis (mild) that resulted in a decrease in XEMBIFY infusion rate to 25 mL/hr/site. All infusion site reactions at higher infusion rates were considered mild in severity.

Study 3
Study 3 was an open-label, multicenter, Phase 4 study conducted in the United States, which included two study arms. The treatment-experienced arm consisted of a single-sequence crossover of weekly-to-biweekly XEMBIFY dosing designed to evaluate the pharmacokinetic non-inferiority and safety of XEMBIFY administered every 2 weeks in treatment-experienced patients with PI. The treatment-naïve arm consisted of a loading regimen followed by weekly maintenance infusions of XEMBIFY to evaluate pharmacokinetics and safety for treatment-naïve patients initiating IgG replacement therapy for the first time.

Patients in the treatment-experienced arm received weekly XEMBIFY dosing initially and transitioned to biweekly dosing at Week 16 through Week 32. A dose adjustment factor of 1.37 was employed for patients entering this study on commercial IVIG. Patients in the treatment-naïve arm initiated IgG replacement therapy for the first time with XEMBIFY (5-day loading regimen 150 mg/kg/day followed by weekly 150 mg/kg/week); dose adjustment in the maintenance phase was allowed to achieve a target IgG trough of 700 mg/dL. Pharmacokinetic assessments were to assess XEMBIFY exposure for both treatment-experienced and treatment-naïve patients.

Thirty-three adults with PI were treated with XEMBIFY in Study 3, including 27 treatment-experienced patients and 6 treatment-naïve patients, all of whom were White and non-Hispanic/Latino. During the study 4 patients discontinued, including 3 treatment-experienced patients (2 for adverse events), and 1 treatment-naïve patient. Two treatment-experienced patients discontinued during the weekly phase and did not receive biweekly XEMBIFY.

For treatment-experienced patients during the weekly dosing period, the median XEMBIFY dose was 138 mg/kg/week ranging from 99 to 247 mg/kg/week, with a median treatment duration of 16 weeks. During the biweekly (every 2 weeks) dosing period, the median dose was 273 mg/kg/2 weeks ranging from 134 to 494 mg/kg/2 weeks, with a median treatment duration of 18 weeks.

For treatment-naïve patients the median XEMBIFY dose was 153 mg/kg per infusion ranging from 150 to 180 mg/kg per infusion with a median treatment duration of 32 weeks.

XEMBIFY exposure was similar between weekly and biweekly dosing in the treatment-experienced patients [see Clinical Pharmacology (12.3)].

Target IgG trough levels were achieved following the loading dose and maintenance dose regimen in treatment-naïve patients [see Clinical Pharmacology (12.3)].

15 REFERENCES

1. Buckley RH, Schiff RI. The use of intravenous immune globulin in immunodeficiency diseases. N Engl J Med 1991;325(2):110-7.
2. Cunningham-Rundles C, Bodian C. Common variable immunodeficiency: clinical and immunological features of 248 patients. Clin Immunol 1999;92(1):34-48.
3. Pruzanski W, Sussman G, Dorian W, et al. Relationship of the dose of intravenous gammaglobulin to the prevention of infections in adults with common variable immunodeficiency. Inflammation 1996;20(4):353-9.
4. Stephan JL, Vlekova V, Le Deist F, et al. Severe combined immunodeficiency: a retrospective single-center study of clinical presentation and outcome in 117 patients. J Pediatr 1993;123(4):564-72.
5. Dalakas MC. High-dose intravenous immunoglobulin and serum viscosity: risk of precipitating thromboembolic events. Neurology 1994;44:223-6.
6. Woodruff RK, Grigg AP, Firkin FC, et al. Fatal thrombotic events during treatment of autoimmune thrombocytopenia with intravenous immunoglobulin in elderly patients. Lancet 1986;2:217-8.
7. Wolberg AS, Kon RH, Monroe DM, et al. Coagulation factor XI is a contaminant in intravenous immunoglobulin preparations. Am J Hematol 2000;65:30-4.
8. Cayco AV, Perazella MA, Hayslett JP. Renal insufficiency after intravenous immune globulin therapy: a report of two cases and an analysis of the literature. J Am Soc Nephrol 1997;8(11):1788-94.
9. Pierce LR, Jain N. Risks associated with the use of intravenous immunoglobulin. Trans Med Rev 2003;17:241-51.
10. Copelan EA, Strohm PL, Kennedy MS, et al. Hemolysis following intravenous immune globulin therapy. Transfusion 1986;26:410-2.
11. Thomas MJ, Misbah SA, Chapel HM, et al. Hemolysis after high-dose intravenous Ig. Blood 1993;15:3789.
12. Wilson JR, Bhoopalam N, Fisher M. Hemolytic anemia associated with intravenous immunoglobulin. Muscle & Nerve 1997;20:1142-5.
13. Kessary-Shoham H, Levy Y, Shoenfeld Y, et al. In vivo administration of intravenous immunoglobulin (IVIg) can lead to enhanced erythrocyte sequestration. J Autoimmun 1999;13:129-35.
14. Kahwaji J, Barker E, Pepkowitz S, et al. Acute hemolysis after high-dose intravenous immunoglobulin therapy in highly HLA sensitized patients. Clin J Am Soc Nephrol 2009;4:1993-7.
15. Daw Z, Padmore R, Neurath D, et al. Hemolytic transfusion reactions after administration of intravenous immune (gamma) globulin: A case series analysis. Transfusion 2008;48:1598-601.
16. Rizk A, Gorson KC, Kenney L, et al. Transfusion-related acute lung injury after the infusion of IVIG. Transfusion 2001;41:264-8.

16 HOW SUPPLIED/STORAGE AND HANDLING

XEMBIFY is supplied in 1, 2, 4, and 10 grams of protein in single use vials.

Package NDC Number | Container NDC Number | Size | Grams of Protein
13533-810-05 | 13533-810-06 | 5 mL | 1
13533-810-10 | 13533-810-11 | 10 mL | 2
13533-810-20 | 13533-810-21 | 20 mL | 4
13533-810-50 | 13533-810-51 | 50 mL | 10

Components used in the packaging are not made with natural rubber latex and contain no preservative.

Store XEMBIFY at 2–8°C (36–46°F).

Note: XEMBIFY may be stored at temperatures not to exceed 25°C (77°F) for up to 6
months any time prior to the expiration date. Following 25°C (77°F) storage, use the
product immediately or discard.

Do not freeze.

Do not use solutions that have been frozen.

Do not use after expiration date.

Discard unused portion.

17 PATIENT COUNSELING INFORMATION

Advise the patient to read the FDA-approved patient labeling (Patient Information and Instructions for Use).

Ask about a history of IgA deficiency, and hypersensitivity reactions to immune globulin treatment. [see Warnings and Precautions (5.3)]

Inform patients to immediately report the following signs and symptoms to their healthcare provider: [see Boxed Warning and Warnings and Precautions]

Severe headache, neck stiffness, drowsiness, dizziness, fever, sensitivity to light, painful
eye movements, nausea, and vomiting [see Warnings and Precautions (5.1),
Adverse Reactions (6.2)]

Symptoms of thrombosis which may include: pain and/or swelling of an arm or leg with
warmth over the affected area, discoloration of an arm or leg, unexplained shortness
of breath, chest pain or discomfort that worsens on deep breathing, unexplained rapid pulse,
numbness or weakness on one side of the body [see Warnings and Precautions (5.2)]

Hypersensitivity reaction including hives, generalized urticaria, itching, rash, tightness of
the chest, wheezing, low blood pressure, and anaphylaxis [see Warnings and Precautions (5.3),
Adverse Reactions (6.2)]

Decreased urine output, sudden weight gain, fluid retention/edema, and/or shortness of
breath [see Warnings and Precautions (5.4)]

Increased heart rate, fatigue, yellowing of the skin or eyes, and dark-colored urine [see
Warnings and Precautions (5.5)]

Trouble breathing, chest pain, pain, blue lips or extremities, chills, and fever [see
Warnings and Precautions (5.6)]

Injection site reactions such as induration and warmth [see Adverse Reactions (6.2)]

Inform patients/caregivers that because XEMBIFY is made from human blood, it may carry a risk of transmitting infectious agents, e.g., viruses, the variant Creutzfeldt-Jakob disease (vCJD) agent and, theoretically, the Creutzfeldt-Jakob disease (CJD) agent. [see Warnings and Precautions (5.7)]

Inform patients that XEMBIFY can interfere with their immune response to live virus vaccines such as measles, mumps, rubella, and varicella. Inform patients to notify their healthcare provider of this potential interaction when they are receiving vaccinations. [see Drug Interactions (7.2)]

Self-administration

Advise the patient to read the FDA-approved patient labeling (Patient Information and Instructions for Use).

If self-administration is deemed appropriate by the healthcare provider, provide clear instructions and training on subcutaneous infusion to the patient/caregiver, and document demonstration of their ability to independently administer subcutaneous infusions.

Ensure the patient/caregiver understands the importance of consistent subcutaneous infusions to maintain appropriate steady IgG levels.

Tell the patient/caregiver to start the infusion promptly after withdrawing XEMBIFY into the syringe. Ensure the patient/caregiver understands that administration should be completed within 2 hours to avoid the potential formation of particles caused by siliconized syringes.

Instruct patient to rotate infusion sites for subsequent infusions.

Instruct the patient/caregiver to keep a treatment diary/log book. This diary/log book should include information about each infusion such as, the time, date, dose, lot number(s), infusion sites, and any reactions.

Inform the patient that mild to moderate local infusion site reactions (e.g., pain, redness and itching) are a common side effect of subcutaneous treatment, but to contact their healthcare provider if a local reaction increases in severity or persists for more than a few days.

Instruct patient to return to the healthcare facility for evaluation at regular intervals so IgG levels can be checked in order to ensure IgG trough levels are adequate.

Manufactured by:
Grifols Therapeutics LLC
Research Triangle Park, NC 27709 USA
U.S. License No. 1871 3067886

INFORMATION FOR PATIENTS

XEMBIFY®
(immune globulin subcutaneous, human-klhw) 20% solution

The following summarizes important information about XEMBIFY (zem-ba-fi). Please read this information carefully before using this medicine. This patient information does not take the place of talking with your healthcare provider about your medical condition or your treatment, and it does not include all of the important information about XEMBIFY. If you have any questions after reading this, contact your healthcare provider.

What is XEMBIFY?

XEMBIFY is a ready-to-use, liquid medicine that contains immunoglobulin G (IgG) antibodies, which protect the body against infection. XEMBIFY is used to treat patients with primary immunodeficiency disease (PI).

There are many forms of PI. The most common types of PI result in an inability to make a very important type of protein called antibodies, which help the body fight off infections from bacteria or viruses. XEMBIFY is made from human plasma that is donated by healthy people. It contains antibodies collected from these healthy people that replace the missing antibodies in PI patients.

Who should NOT use XEMBIFY?

Do not use XEMBIFY if you have a known history of severe allergic reaction to immune globulin (human) or other blood products. If you have such a history, discuss this with your healthcare provider to determine if XEMBIFY is right for you.

Tell your healthcare provider if you have or ever had:

- a serious reaction to other medicines that contain immune globulin.
- an immunoglobulin A (IgA) deficiency.
- a history of heart or blood vessel disease.
- blood clots or “thick blood”.
- inability to move for some time.

How should I take XEMBIFY?

XEMBIFY is given under the skin (subcutaneously). Most of the time, infusions under the skin are given at home by self-infusion or by infusion with a caregiver’s help. Self-infusion is different from giving yourself a shot.

Instructions for taking XEMBIFY are at the end of this patient information. [see "Instructions for Use"] Only use XEMBIFY by yourself after you have been instructed by your healthcare provider.

What should I tell my healthcare provider before using XEMBIFY?

Tell your healthcare provider if you have had a serious reaction to other medicines that contain immune globulin. Also tell your healthcare provider if you have an immunoglobulin A (IgA) deficiency.

XEMBIFY can make certain types of vaccines (like measles/mumps/rubella or chickenpox) not work as well for you. Before you get a vaccine, tell the healthcare provider that you are taking XEMBIFY.

Tell your healthcare provider if you are pregnant or plan to become pregnant, or if you are nursing.

What are possible or reasonably likely side effects of XEMBIFY?

The most common side effects with XEMBIFY are:
Infusion site reactions, including but not limited to
infusion site erythema (redness)
infusion site pain
infusion site swelling (puffiness)
infusion site bruising
infusion site nodule
infusion site pruritus (itching)
infusion site induration (firmness)
infusion site scab
infusion site edema
Cough
Diarrhea

If any of the following problems occur after starting treatment with XEMBIFY, stop the infusion immediately and contact your healthcare provider or call emergency services. These could be signs of a serious problem.

Hives, swelling in the mouth or throat, itching, trouble breathing, wheezing, fainting or dizziness.
These could be signs of a serious allergic reaction.

Severe headache with or without nausea, vomiting, stiff neck, fever, sensitivity to light, painful eye movements, or fatigue.
These could be signs of irritation of the lining around your brain called aseptic meningitis.

Reduced urination, sudden weight gain, or swelling in your legs. These could be signs of a kidney problem.

Pain, swelling, warmth, redness, or a lump in your legs or arms. These could be signs of a blood clot.

Brown or red urine, fast heart rate, yellow skin or eyes. These could be signs of a liver problem or a blood problem.

Chest pain or trouble breathing, or blue lips or extremities. These could be signs of a serious heart or lung problem.

Fever over 100°F (37.8oC). This could be a sign of an infection.

Tell your healthcare provider about any side effects that concern you. You can ask your healthcare provider to give you the full prescribing information available to healthcare providers. You are encouraged to report side effects to Grifols Therapeutics LLC [1-800-520-2807].

How do I store XEMBIFY?

XEMBIFY comes in single use vials.

- Keep XEMBIFY refrigerated. Do not freeze.
- If needed, you can store XEMBIFY at room temperature for up to 6 months, but you must use it within that time or you must throw it away.
- Do not return XEMBIFY to the refrigerator if it was warmed to room temperature.
- Check the expiration date on the carton and vial label.
- Do not use XEMBIFY after the expiration date.

What else should I know about XEMBIFY?

Do not use XEMBIFY for a medical condition for which it was not prescribed. Do not share XEMBIFY with other people, even if they have the same diagnosis and symptoms that you have.

INSTRUCTIONS FOR USE

Infuse XEMBIFY only after you have been trained by your healthcare provider. Below are step-by-step instructions to help you remember how to use XEMBIFY. Ask your healthcare provider about any instructions you do not understand.

Before Using XEMBIFY

Prior to use, allow the solution to come to room temperature (68-77°F or 20-25°C). This can take 60 minutes or longer.

Do not apply heat or place in the microwave.

Step 1: Assemble supplies

Gather the XEMBIFY vial(s), ancillary supplies, sharps container, patient’s treatment diary/logbook, and the infusion pump.

Step 2: Clean surface

Set up your infusion area on a clean, flat, non-porous surface, such as a kitchen counter.

Avoid using porous surfaces such as wood. Clean the surface with an alcohol wipe using a circular motion from the center outward.

Step 3: Wash hands

Wash and dry your hands thoroughly before using XEMBIFY.

Your healthcare provider may recommend that you use antibacterial soap or that you wear gloves.

Step 4: Check vials

The liquid in the vial should be clear to slightly opalescent, and colorless or pale yellow.

Do not use the vial if:

- the solution is cloudy or discolored. The solution should be clear to slightly opalescent, and colorless or pale yellow.
- the protective cap is missing, or there is any evidence of tampering. Tell your healthcare provider immediately.
- the expiration date has passed.

Step 5: Remove the protective cap

Remove the protective cap from the vial to expose the middle of the stopper.

Wipe the stopper with alcohol and allow to dry.

Step 6: Transfer XEMBIFY from vial(s) to syringe

Do not allow your fingers or other objects to touch the inner stem of the plunger, the syringe tip, or other areas that can touch the XEMBIFY solution. Make sure needles are capped until used and that needles and syringes stay on the clean area created in Step 2. This is called “aseptic technique” to prevent germs from getting into the XEMBIFY.

Using aseptic technique, attach each needle to the syringe tip.

Step 7: Prepare the syringe and draw XEMBIFY solution into syringe

Remove cap from needle.

Pull the syringe plunger back to the level matching the amount of XEMBIFY to be withdrawn from the vial.

Place the XEMBIFY vial on a clean flat surface and insert the needle into the center of the vial stopper.

Inject air into the vial. The amount of air should match the amount of XEMBIFY to be withdrawn.

Turn the vial upside down and withdraw the correct amount of XEMBIFY. If multiple vials are required to get the correct dose, repeat Steps 4-7.

Step 8: Fill the pump reservoir and prepare the infusion pump

Follow the pump manufacturer’s instructions for filling the pump reservoir and preparing the infusion pump, administration tubing and Y-site connection tubing, if needed.

Prime the administration tubing with XEMBIFY to take out any air left in the tubing or needle. To prime, hold the syringe in one hand and the administration tubing’s capped needle in the other. Gently squeeze on the plunger until you see a drop of XEMBIFY come out of the needle.

Step 9: Select the number and location of infusion sites

Select one or more infusion sites as directed by your healthcare provider. The number and location of injection sites depends on the volume of the total dose.

Avoid: bony areas, visible blood vessels, scars, and any areas of inflammation (irritation) or infection.

Rotate sites between future infusions.

Step 10: Prepare the infusion site

Wipe the infusion site(s) with a sterile alcohol wipe beginning at the center of each infusion site and moving outward in circular motion. Allow the infusion site(s) to dry (at least 30 seconds).

Before infusion, sites should be clean, dry, and at least 2 inches (5 cm) apart.

Step 11: Insert the needle

Grasp the skin between two fingers (pinch at least 1 inch (2.5 cm) of skin) and insert the needle at a 90-degree angle into the tissue underneath the skin or subcutaneous tissue.

Step 12: Make sure the needle is not in a blood vessel

After inserting each needle into tissue (and before your infusion), make sure that a blood vessel has not been accidentally entered. To do this, attach a sterile syringe to the end of the primed administration tubing. Pull back on the syringe plunger and watch for any blood flowing back into administration tubing.

If you see any blood, remove and discard the needle and administration tubing.

Repeat priming and needle insertion steps using a new needle, administration tubing and a new infusion site.

Secure the needle in place by applying sterile gauze or transparent dressing over the site.

Step 13: Repeat for other sites, as needed

Step 14: Infuse XEMBIFY

Infuse XEMBIFY as soon as possible after it is prepared.

Follow the pump manufacturer’s instructions for filling the tubing and using the infusion pump.

Step 15: After infusion

Follow manufacturer’s instructions to turn off pump.

Undo and discard any dressing or tape.

Gently remove the inserted needle(s) or catheter(s).

Discard any unused solution in an appropriate waste container as instructed.

Discard any used administration equipment in an appropriate waste container.

Store your supplies in a safe place.

Follow manufacturer’s instructions to care for the infusion pump.

Step 16: Record each infusion

Remove the peel-off label with the product lot number from the XEMBIFY vial and use this to complete the patient record. Include information about each infusion such as: the time, date, dose, lot number(s), infusion sites, and any reactions.

Remember to bring your journal with you when you visit your healthcare provider. Your healthcare provider may ask to see your treatment diary/logbook.

Tell your healthcare provider about any problems you have during your infusions. Call your healthcare provider for medical advice about side effects. You can also report side effects to FDA at 1-800-FDA-1088 or www.fda.gov/medwatch.

Manufactured by:
Grifols Therapeutics LLC
Research Triangle Park, NC 27709 USA
U.S. License No. 1871 Revised 7/2024
3067886

PACKAGE LABEL

NDC 13533-810-50
10 g / 50 mL
Immune Globulin
Subcutaneous,
Human - klhw, 20%
Xembify®
Solution for Subcutaneous Administration
Rx only
GRIFOLS
Contents:
One vial of Xembify®
No preservative
Sterile, Non-pyrogenic
Xembify® may be stored at 2–8°C (36–
46°F), AND product may be stored at
temperatures not to exceed 25°C (77°F)
for up to 6 months anytime prior to the
expiration date, after which the product
must be immediately used or discarded.
Do not freeze.
Date removed from refrigeration:
GRIFOLS
Refer to package insert for dosage
and administration.
Single Use Vial
Do not use if turbid.
Discard unused portion. Do not store
after entry into vial.
Each milliliter (mL) contains approxi-
mately 200 mg of protein, not less
than 98% of which is gamma
globulin, and approximately 15 mg
glycine and 25 mcg polysorbate 80.
Do not use the product if it shows
any signs of tampering and notify
Grifols Therapeutics LLC immediately.
Grifols Therapeutics LLC
Research Triangle Park,
NC 27709 USA
U.S. License No. 1871
GRIFOLS
GRIFOLS
GTIN (01)00313533810504
LOT XXXXXXXXXX
EXP DDMMMYYYY
SN XXXXXXXXXXXXXXXX
Immune Globulin
Subcutaneous,
Human – klhw, 20%
Xembify®
Carton: 3057222

NDC 13533-810-51
10 g / 50 mL
Immune Globulin
Subcutaneous,
Human - klhw, 20%
Xembify®
Solution for
subcutaneous administration
Rx Only
GRIFOLS
Refer to package insert for dosage and administration and compatibility
with other solutions.
Xembify® may be stored at 2–8°C (36–46°F), AND product may be stored at
temperatures not to exceed 25°C (77°F) for up to 6 months anytime prior to
the expiration date, after which the product must be immediately used or
discarded.
Single Use Vial, Discard unused portion
Do not use if turbid.
Grifols Therapeutics LLC
Research Triangle Park, NC 27709 USA
U.S. License No. 1871
Xembify® 10 g Protein in 50 mL PULL
Lot
3057120
Lot
Exp.